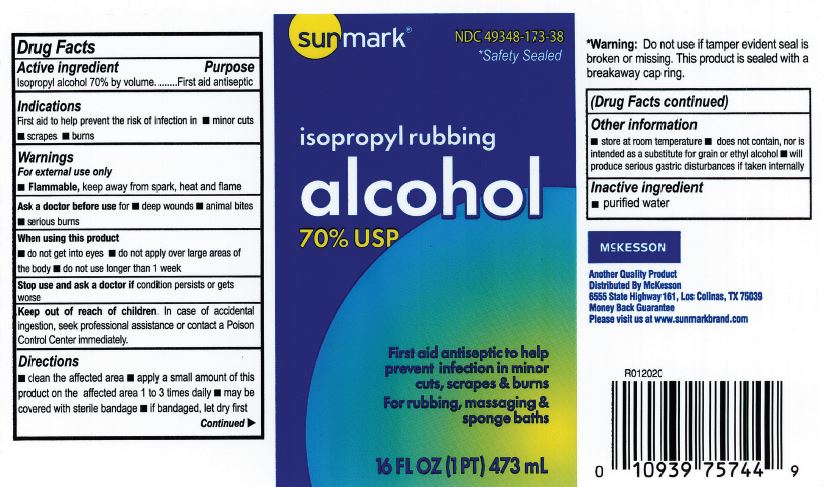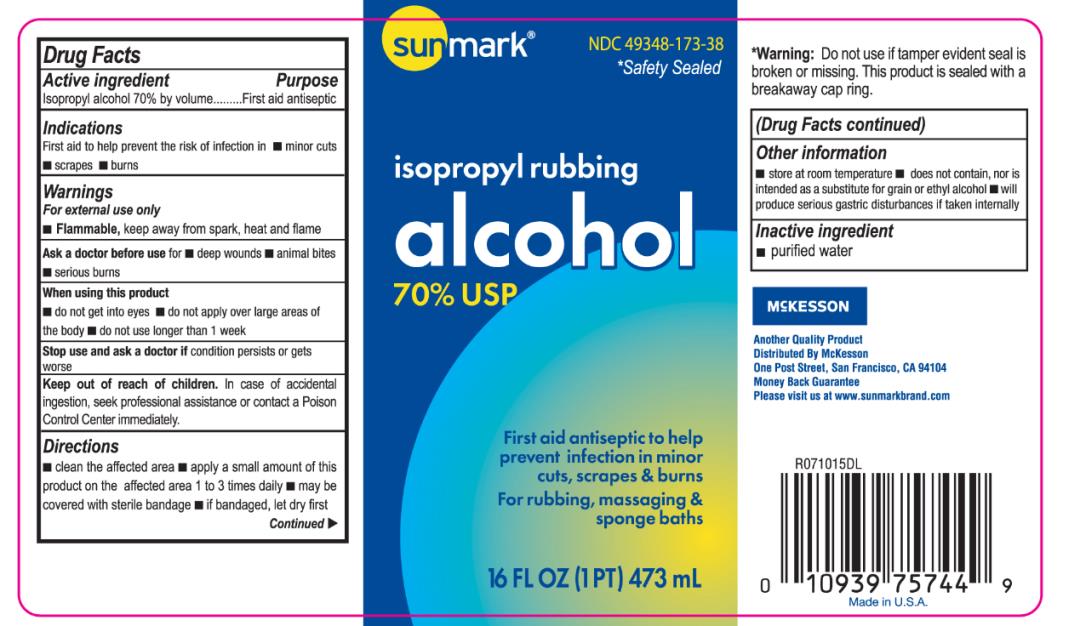 DRUG LABEL: Sunmark Isopropyl Rubbing Alcohol 70 Percent
NDC: 49348-173 | Form: LIQUID
Manufacturer: Strategic Sourcing Services LLC
Category: otc | Type: HUMAN OTC DRUG LABEL
Date: 20200621

ACTIVE INGREDIENTS: ISOPROPYL ALCOHOL 700 mg/1 mL
INACTIVE INGREDIENTS: WATER

Sunmark Isopropyl Rubbing Alcohol 70 Percent USP

Drug Facts

Active Ingredient

Isopropyl Alcohol 70% by volume

Purpose

First aid antiseptic

Use

First aid to help prevent the risk of infection in.

- minor cuts
- scrapes
- burns

Warnings

For external use only.

- Flammable, keep way from spark, heat and flame.
- Use in well ventilated area, fumes may be harmful.

Ask a doctor before use for

- deep wounds
- animal bites
- serious burns

When using this product

- do not get into eyes or mucous membranes.
- do not apply to irritated skin.

Stop use and ask a doctor if

excessive irritation of the skin develops.

Keep out of reach of children.

In case of accidental ingestion, seek professional assistance or contact a Poison Control Center immediately.

Directions

- clean the affected area.
- apply a small amount of this product on the affected area 1 to 3 times daily.
- may be covered with sterile bandage.
- if bandaged, let it dry first.

Other Information

- store at room temperature
- does not contain, nor is intended as a substitute for grain or ethyl alcohol.
- will produce serious gastric disturbances if taken internally.

Inactive Ingredient

purified water

Principal Display Panel

NDC 49348-173-38
isopropyl rubbing
alcohol
70% USP
16 FL OZ (1 PT) 473 mL